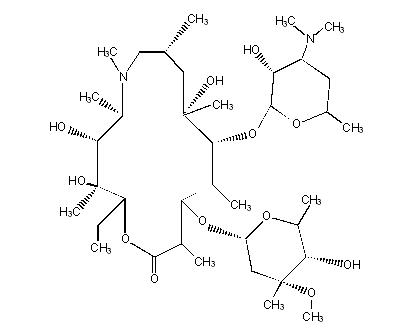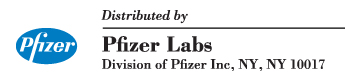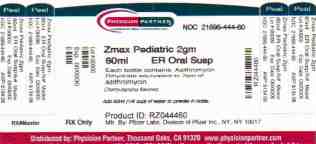 DRUG LABEL: Zmax
NDC: 21695-444 | Form: POWDER, FOR SUSPENSION
Manufacturer: Rebel Distributors Corp
Category: prescription | Type: HUMAN PRESCRIPTION DRUG LABEL
Date: 20110126

ACTIVE INGREDIENTS: azithromycin 2 g/60 mL
INACTIVE INGREDIENTS: glyceryl behenate; poloxamer 407; sucrose; sodium phosphate, tribasic anhydrous; magnesium hydroxide; hydroxypropyl cellulose; xanthan gum; silicon dioxide; titanium dioxide

HIGHLIGHTS OF PRESCRIBING INFORMATION

These highlights do not include all the information needed to use ZMAX safely and effectively. See full prescribing information for ZMAX.
ZMAX (azithromycin) powder, for suspension for oral use
Initial U.S. Approval: 1991

RECENT MAJOR CHANGES

Indication and Usage, Community-acquired pneumonia (1) | 9/2008
Pediatric patients (6 months and older)
Dosage and Administration, Pediatric patients (2.2) | 9/2008
Warnings and Precautions, Exacerbation of myasthenia gravis (5.3) | 9/2008

1 INDICATIONS AND USAGE

Zmax is a macrolide antimicrobial indicated for mild to moderate infections caused by designated, susceptible bacteria:

- Acute bacterial sinusitis in adults (1)
- Community-acquired pneumonia in adults and children 6 months and older (1)

2 DOSAGE AND ADMINISTRATION

- Adults: 2 g as a single dose; consume contents of full bottle (2.1)
- Pediatric: 60 mg/kg (1 mL of suspension per pound body weight; equivalent to 27 mg/lb) as a single dose, up to a maximum of 2 g (2.2)

3 DOSAGE FORMS AND STRENGTHS

Bottle containing 2 g azithromycin for constitution with 60 mL of water (final concentration 27 mg/mL) (3)

4 CONTRAINDICATIONS

Hypersensitivity to azithromycin, erythromycin, or any macrolide or ketolide antibiotic (4)

5 WARNINGS AND PRECAUTIONS

- Severe (including fatal) allergic and skin reactions: Discontinue Zmax if reaction occurs. (5.1)
- Clostridium difficile-associated diarrhea: Evaluate patients if diarrhea occurs. (5.2)
- Exacerbation of myasthenia gravis (5.3)
- Gastrointestinal Disturbances: higher incidence in patients with GFR<10 mL/min. (5.4)

6 ADVERSE REACTIONS

Most common adverse reactions (incidence ≥1%) are diarrhea/loose stools, nausea, abdominal pain, headache, and vomiting (6.1, 6.2)

To report SUSPECTED ADVERSE REACTIONS, contact Pfizer, Inc at 1-800-438-1985 or FDA at 1-800-FDA-1088 or www.fda.gov/medwatch

7 DRUG INTERACTIONS

Warfarin: Use with azithromycin may increase coagulation times; monitor prothrombin time (7)

8 USE IN SPECIFIC POPULATIONS

Pediatric use:

- Safety and efficacy in the treatment of patients under 6 months of age have not been established. (8.4)

FULL PRESCRIBING INFORMATION

To reduce the development of drug-resistant bacteria and maintain the effectiveness of Zmax and other antibacterial drugs, Zmax should be used only to treat infections that are proven or strongly suspected to be caused by susceptible bacteria.

1 INDICATIONS AND USAGE

Zmax is indicated for the treatment with mild to moderate infections caused by susceptible isolates of the designated microorganisms in the specific conditions listed below. [See CLINICAL STUDIES (14)]

Acute bacterial sinusitis in adults due to Haemophilus influenzae, Moraxella catarrhalis or Streptococcus pneumoniae.

Community-acquired pneumonia in adults and pediatric patients six months of age or older due to Chlamydophila pneumoniae, Haemophilus influenzae, Mycoplasma pneumoniae or Streptococcus pneumoniae, in patients appropriate for oral therapy. Pediatric use in this indication is based on extrapolation of adult efficacy. [See USE IN SPECIFIC POPULATIONS (8.4)]

To reduce the development of drug-resistant bacteria and maintain the effectiveness of Zmax and other antibacterial drugs, Zmax should be used only to treat infections that are proven or strongly suspected to be caused by susceptible bacteria. When culture and susceptibility information are available, they should be considered in selecting or modifying antibacterial therapy. In the absence of such data, local epidemiology and susceptibility patterns may contribute to the empiric selection of therapy.

Appropriate culture and susceptibility tests should be performed before treatment to determine the causative organism and its susceptibility to Zmax. [See Clinical Pharmacology (12.4)] Therapy with Zmax may be initiated before results of these tests are known; once the results become available, antimicrobial therapy should be adjusted accordingly.

2 DOSAGE AND ADMINISTRATION

2.1 Adults

Zmax should be taken as a single 2 g dose. Zmax provides a full course of antibacterial therapy in a single oral dose. It is recommended that Zmax be taken on an empty stomach (at least 1 hour before or 2 hours following a meal).

2.2 Pediatric patients

For pediatric patients 6 months and older, Zmax should be taken as a single dose of 60 mg/kg (equivalent to 27 mg/lb) body weight. The Zmax dose in mL is equivalent to the child's weight in lb (1 mL/lb dose, see Table 1 below), for a body weight of less than 75 lb (34 kg). It is recommended that Zmax be taken on an empty stomach (at least 1 hour before or 2 hours following a meal).

Pediatric patients weighing 75 lb (34 kg) or more should receive the adult dose (2 g).

Table 1. Zmax Pediatric Dosage Guidelines: 1-dose regimen
Dosing Calculated on 1 mL/lb, Dose 1 mL of Suspension for every 1 lb of Body Weight for Children <75 lb (34 kg) [To ensure accurate dosing, a dosing spoon, medicine syringe, or cup is recommended.]
Weight |  | 1 mL/lb Dose
Lb | Kg | Dose | Volume
Lb | Kg | (mg) | (mL)
10 | 5 | 270 | 10
15 | 7 | 405 | 15
20 | 9 | 540 | 20
25 | 11 | 675 | 25
30 | 14 | 810 | 30
35 | 16 | 945 | 35
40 | 18 | 1080 | 40
45 | 20 | 1215 | 45
50 | 23 | 1350 | 50
55 | 25 | 1485 | 55
60 | 27 | 1620 | 60
65 | 30 | 1755 | 65
70 | 32 | 1890 | 70
≥75 | 34 | 2000 | Consume entire contents of bottle

2.3 Additional treatment after vomiting with Zmax

In the event that a patient vomits within 5 minutes of administration, the health care provider should consider additional antibiotic treatment since there would be minimal absorption of azithromycin. Since insufficient data exist on absorption of azithromycin if a patient vomits between 5 and 60 minutes following administration, alternative therapy should be considered. Neither a second dose of Zmax nor alternative treatment is warranted if vomiting occurs ≥60 minutes following administration, in patients with normal gastric emptying. In patients with delayed gastric emptying, alternative therapy should be considered.

2.4 Instructions for the pharmacist

Constitute with 60 mL of water and replace cap. Shake bottle well before dispensing. Do not refrigerate. Constituted suspension should be consumed within 12 hours.

For pediatric dosing in patients weighing less than 75 lb (34 kg), use of a dosing device is recommended. The pharmacist should inform the patient's caregiver that any suspension remaining after dosing MUST be discarded.

3 DOSAGE FORMS AND STRENGTHS

Each bottle of Zmax contains azithromycin dihydrate equivalent to 2 g of azithromycin. After constitution with 60 mL of water, each mL of suspension contains 27 mg of azithromycin. The suspension is a white or off-white color and has a cherry/banana flavor.

4 CONTRAINDICATIONS

Zmax is contraindicated in patients with known hypersensitivity to azithromycin, erythromycin or any macrolide or ketolide antibiotic. [SEE WARNINGS AND PRECAUTIONS (5.1)]

5 WARNINGS AND PRECAUTIONS

5.1 Allergic and skin reactions

Serious allergic reactions, including angioedema, anaphylaxis, Stevens Johnson syndrome and toxic epidermal necrolysis have been reported rarely in patients on azithromycin therapy using other formulations. Although rare, fatalities have been reported. Despite initially successful symptomatic treatment of the allergic symptoms, when symptomatic therapy was discontinued, the allergic symptoms recurred soon thereafter in some patients without further azithromycin exposure. These patients required prolonged periods of observation and symptomatic treatment. The relationship of these episodes to the long tissue half-life of azithromycin and subsequent exposure to antigen has not been determined.

If an allergic reaction occurs, appropriate therapy should be instituted. Physicians should be aware that reappearance of the allergic symptoms may occur when symptomatic therapy is discontinued.

5.2 Clostridium difficile-associated diarrhea

Clostridium difficile-associated diarrhea (CDAD) has been reported with use of nearly all antibacterial agents, including Zmax, and may range in severity from mild diarrhea to fatal colitis. Treatment with antibacterial agents alters the normal flora of the colon leading to overgrowth of C. difficile.

C. difficile produces toxins A and B which contribute to the development of CDAD. Hypertoxin producing strains of C. difficile cause increased morbidity and mortality, as these infections can be refractory to antimicrobial therapy and may require colectomy. CDAD must be considered in all patients who present with diarrhea following antibiotic use. Careful medical history is necessary since CDAD has been reported to occur over two months after the administration of antibacterial agents.

If CDAD is suspected or confirmed, ongoing antibiotic use not directed against C. difficile may need to be discontinued. Appropriate fluid and electrolyte management, protein supplementation, antibiotic treatment of C. difficile, and surgical evaluation should be instituted as clinically indicated.

5.3 Exacerbation of myasthenia gravis

Exacerbation of symptoms of myasthenia gravis and new onset of myasthenic syndrome have been reported in patients receiving azithromycin therapy.

5.4 Gastrointestinal Disturbances

A higher incidence of gastrointestinal adverse events (8 of 19 subjects) was observed when Zmax was administered to a limited number of subjects with GFR< 10 mL/min [See USE IN SPECIFIC POPULATIONS (8.6)]

5.5 Prolongation of the QT interval

Prolonged cardiac repolarization and QT interval, imparting a risk of developing cardiac arrhythmia and torsades de pointes, have been seen in treatment with other macrolides. A similar effect with azithromycin cannot be completely ruled out in patients at increased risk for prolonged cardiac repolarization.

5.6 Development of drug resistant bacteria

Prescribing Zmax in the absence of a proven or strongly suspected bacterial infection is unlikely to provide benefit to the patient and increases the risk of the development of drug-resistant bacteria.

6 ADVERSE REACTIONS

6.1 Clinical studies experience

Because clinical trials are conducted under widely varying conditions, adverse reaction rates observed in the clinical trials of a drug cannot be directly compared to rates in the clinical trials of another drug and may not reflect the rates observed in practice.

Adults:

The data described below reflect exposure to Zmax in 728 adult patients. All patients received a single 2 g oral dose of Zmax. The population studied had community-acquired pneumonia and acute bacterial sinusitis.

In controlled clinical trials with Zmax, the majority of the reported treatment-related adverse reactions were gastrointestinal in nature and mild to moderate in severity.

Overall, the most common treatment-related adverse reactions in adult patients receiving a single 2 g dose of Zmax were diarrhea/loose stools (12%), nausea (4%), abdominal pain (3%), headache (1%), and vomiting (1%). The incidence of treatment-related gastrointestinal adverse reactions was 17% for Zmax and 10% for pooled comparators.

Treatment-related adverse reactions following Zmax treatment that occurred with a frequency of <1% included the following:

Cardiovascular: palpitations, chest pain
Gastrointestinal: constipation, dyspepsia, flatulence, gastritis, oral moniliasis
Genitourinary: vaginitis
Nervous System: dizziness, vertigo
General: asthenia
Allergic: rash, pruritus, urticaria
Special Senses: taste perversion

Laboratory Abnormalities

In subjects with normal baseline values, the following clinically significant laboratory abnormalities (irrespective of drug relationship) were reported in Zmax clinical trials:

- -with an incidence of greater than or equal to 1%: reduced lymphocytes and increased eosinophils; reduced bicarbonate;
- -with an incidence of less than 1%: leukopenia, neutropenia, elevated bilirubin, AST, ALT, BUN, creatinine, alterations in potassium.

Where follow-up was provided, changes in laboratory tests appeared to be reversible.

Pediatric Patients:

The data described below reflect exposure to Zmax in 907 pediatric patients. The population was 3 months to 12 years of age. All patients received a single 60 mg/kg oral dose of Zmax.

As in adults, the most common treatment-related adverse reactions in pediatric subjects were gastrointestinal in nature. The pediatric subjects all received a single 60 mg/kg dose (equivalent to 27 mg/lb) of Zmax.

In a study with 450 pediatric subjects (ages 3 months to 48 months), vomiting (11%), diarrhea (10%) loose stools (9%), and abdominal pain (2%) were the most frequently reported treatment-related gastrointestinal adverse reactions. Many treatment related gastrointestinal adverse reactions with an incidence greater than 1% began on the day of dosing in these subjects [43% (68/160)] and most [53% (84/160)] resolved within 48 hours of onset. Treatment-related adverse events that were not gastrointestinal, occurring with a frequency ≥ 1% were: rash (5%), anorexia (2%), fever (2%), and dermatitis (2%).

In a second study of 337 pediatric subjects, ages 2 years to 12 years, the most frequently reported treatment-related adverse reactions also included vomiting (14%), diarrhea (7%), loose stools (2%), nausea (4%) and abdominal pain (4%).

A third study investigated the tolerability of two different concentrations of azithromycin oral suspension in 120 pediatric subjects (ages 3 months to 48 months), all of whom were treated with azithromycin. The study evaluated the hypothesis that a more dilute, less viscous formulation (the recommended 27 mg/mL concentration of Zmax) is less likely to induce vomiting in young children than a more concentrated suspension used in other pediatric studies. The vomiting rate for subjects taking the dilute concentration azithromycin was 3% (2/61). The rate was numerically lower but not statistically different from the vomiting for the more concentrated suspension Across both treatment arms, the only treatment-related adverse events with a frequency of ≥ 1% were vomiting (6%, 7/120) and diarrhea (2%, 2/120).

Treatment-related adverse reactions with a frequency of < 1% following Zmax treatment in all 907 pediatric subjects in the Phase 3 studies were:

Body as a whole: chills, fever, flu syndrome, headache;
Digestive: abnormal stools, constipation, dyspepsia, flatulence, gastritis, gastrointestinal disorder, hepatitis;
Hemic and Lymphatic: leukopenia;
Nervous System: agitation, emotional liability, hostility, hyperkinesia, insomnia, irritability, parasthesia, somnolence;
Respiratory: asthma, bronchitis, cough increased, dyspnea, pharyngitis, rhinitis;
Skin and Appendages: dermatitis, fungal dermatitis, maculopapular rash, pruritus, urticaria;
Special Senses: otitis media, taste perversion;
Urogenital: dysuria.

Laboratory Abnormalities

In subjects with normal baseline values, the following clinically significant laboratory abnormalities (irrespective of drug relationship) were reported in Zmax pediatric clinical trials:

- -with an incidence of greater than or equal to 1%: elevated eosinophils, BUN, and potassium; decreased lymphocytes; and alterations in neutrophils;
- -with an incidence of less than 1%: elevated SGOT, SGPT and creatinine; decreased potassium; and alterations in sodium and glucose.

6.2 Postmarketing experience with other azithromycin products

Because these reactions are reported voluntarily from a population of uncertain size, reliably estimating their frequency or establishing a causal relationship to drug exposure is not always possible.

Adverse events reported with azithromycin immediate release formulations during the postmarketing period for which a causal relationship may not be established include:

Allergic: arthralgia, edema, urticaria and angioedema
Cardiovascular: palpitations and arrhythmias including ventricular tachycardia and hypotension
There have been rare reports of QT prolongation and torsades de pointes.
Gastrointestinal: anorexia, constipation, dyspepsia, flatulence, vomiting/diarrhea rarely resulting in dehydration, pseudomembranous colitis, pancreatitis, oral candidiasis and rare reports of tongue discoloration
General: asthenia, paresthesia, fatigue, malaise and anaphylaxis (rarely fatal)
Genitourinary: interstitial nephritis, acute renal failure, moniliasis and vaginitis
Hematopoietic: thrombocytopenia, mild neutropenia
Liver/Biliary: abnormal liver function including hepatitis and cholestatic jaundice, as well as rare cases of hepatic necrosis and hepatic failure, some of which have resulted in death
Nervous System: convulsions, dizziness/vertigo, headache, somnolence, hyperactivity, nervousness, agitation and syncope
Psychiatric: aggressive reaction and anxiety
Skin/Appendages: pruritus, rash, photosensitivity, rarely serious skin reactions including erythema multiforme, Stevens-Johnson syndrome and toxic epidermal necrolysis
Special Senses: hearing disturbances including hearing loss, deafness and/or tinnitus and rare reports of taste/smell perversion and/or loss

7 DRUG INTERACTIONS

Warfarin

Although, in a study of 22 healthy men, a 5-day course of azithromycin did not affect the prothrombin time from a subsequently administered dose of warfarin, spontaneous post-marketing reports suggest that concomitant administration of azithromycin may potentiate the effects of oral anticoagulants. Prothrombin times should be carefully monitored while patients are receiving azithromycin and oral anticoagulants concomitantly.

8 USE IN SPECIFIC POPULATIONS

8.1 Pregnancy

TERATOGENIC EFFECTS

Teratogenic Effects. Pregnancy Category B: Reproduction studies have been performed in rats and mice at doses up to moderately maternally toxic dose concentrations (i.e., 200 mg/kg/day). These daily doses in rats and mice, based on mg/m^2, are estimated to be approximately equivalent to one or one-half of, respectively, the single adult oral dose of 2 g. In the animal studies, no evidence of harm to the fetus due to azithromycin was found. There are, however, no adequate and well-controlled studies in pregnant women. Because animal reproduction studies are not always predictive of human response, azithromycin should be used during pregnancy only if clearly needed.

8.3 Nursing Mothers

It is not known whether azithromycin is excreted in human milk. Because many drugs are excreted in human milk, caution should be exercised when azithromycin is administered to a nursing woman.

8.4 Pediatric Use

Safety and effectiveness in the treatment of pediatric patients under 6 months of age have not been established.

Community-Acquired Pneumonia: The safety and effectiveness of Zmax have been established in pediatric patients 6 months of age or older with community-acquired pneumonia due to Chlamydophila pneumoniae, Mycoplasma pneumoniae, Haemophilus influenzae or Streptococcus pneumoniae. Use of Zmax for these patients is supported by evidence from adequate and well-controlled studies of Zmax in adults with additional safety and pharmacokinetic data in pediatric patients. [See DOSAGE AND ADMINISTRATION (2.2), ADVERSE REACTIONS (6), CLINICAL PHARMACOLOGY (12.3)]

Acute bacterial sinusitis: Safety and effectiveness in the treatment of pediatric patients with acute bacterial sinusitis have not been established.

8.5 Geriatric Use

Data collected from the azithromycin capsule and tablet formulations indicate that a dosage adjustment does not appear to be necessary for older patients with normal renal function (for their age) and hepatic function receiving treatment with Zmax.

In clinical trials of Zmax, 17% of subjects were at least 65 years of age (214/1292) and 5% of subjects (59/1292) were at least 75 years of age. No overall differences in safety or effectiveness were observed between these subjects and younger subjects.

8.6 Renal Impairment

No dosage adjustment is recommended for patients GFR >10 mL/min. Caution should be exercised when Zmax is administered to patients with GFR <10 mL/min, due to a higher incidence of gastrointestinal adverse events (8 of 19 subjects) observed in a limited number of subjects with GFR <10 mL/min. [See CLINICAL PHARMACOLOGY (12)]

8.7 Gender

The impact of gender on the pharmacokinetics of azithromycin has not been evaluated for Zmax. However, previous studies have demonstrated no significant differences in the disposition of azithromycin between male and female subjects. No dosage adjustment of Zmax is recommended based on gender.

10 OVERDOSAGE

Adverse events experienced in higher than recommended doses were similar to those seen at normal doses. In the event of overdosage, general symptomatic and supportive measures are indicated as required.

11 DESCRIPTION

Zmax (azithromycin extended release) for oral suspension contains the active ingredient azithromycin (as azithromycin dihydrate), an azalide, a subclass of macrolide antibiotics. Azithromycin has the chemical name (2R,3S,4R,5R,8R,10R,11R,12S,13S,14R)13-[(2,6-Dideoxy-3-C-methyl-3-O-methyl-α-L-ribo-hexopyranosyl) oxy]-2-ethyl-3,4,10-trihydroxy-3,5,6,8,10,12,14-heptamethyl-11-[[3,4,6-trideoxy-3- (dimethylamino)-β-D-xylo-hexopyranosyl]oxy]-1-oxa-6-azacyclopentadecan-15-one. Azithromycin is derived from erythromycin; however, it differs chemically from erythromycin in that a methyl-substituted nitrogen atom is incorporated into the lactone ring. Its molecular formula is C38H72N2O12, and its molecular weight is 749.0. Azithromycin has the following structural formula:

Azithromycin, as the dihydrate, is a white crystalline powder with a molecular formula of C38H72N2O12•2H2O and a molecular weight of 785.0.

Zmax is a single-dose, extended release formulation of microspheres for oral suspension containing azithromycin (as azithromycin dihydrate) and the following excipients: glyceryl behenate, poloxamer 407, sucrose, sodium phosphate tribasic anhydrous, magnesium hydroxide, hydroxypropyl cellulose, xanthan gum, colloidal silicon dioxide, titanium dioxide, artificial cherry flavor, and artificial banana flavor.

Note: Each bottle of Zmax 2 g for oral suspension contains approximately 148 mg of sodium and 19 g of sucrose. Constituted Zmax oral suspension contains approximately 2 mg/mL of sodium and 0.26 g/mL of sucrose.

12 CLINICAL PHARMACOLOGY

12.1 Mechanism of Action

Azithromycin is an antimicrobial agent [See Clinical Pharmacology (12.4)]

12.2 Pharmacodynamics

Based on animal models of infection, the antimicrobial activity of azithromycin appears to correlate with the ratio of area under the concentration-time curve to minimum inhibitory concentration (AUC/MIC) for certain pathogens (S. pneumoniae and S. aureus). The principal pharmacokinetic/pharmacodynamic parameter best associated with clinical and microbiological cure has not been elucidated in clinical trials with Zmax.

12.3 Pharmacokinetics

Zmax is an extended release microsphere formulation. Based on data obtained from studies evaluating the pharmacokinetics of azithromycin in healthy adult subjects a higher peak serum concentration (Cmax) and greater systemic exposure (AUC 0–24) of azithromycin are achieved on the day of dosing following a single 2 g dose of Zmax versus 1.5 g of azithromycin tablets administered over 3 days (500 mg/day) or 5 days (500 mg on day 1, 250 mg/day on days 2–5) [Table 2]. Consequently, due to these different pharmacokinetic profiles, Zmax is not interchangeable with azithromycin tablet 3-day and 5-day dosing regimens.

Table 2. Mean (SD) Pharmacokinetic Parameters for Azithromycin on Day 1 Following the Administration of a Single Dose of 2 g Zmax or 1.5 g of Azithromycin Tablets Given over 3 Days (500 mg/day) or 5 Days (500 mg on Day 1 and 250 mg on Days 2–5) to Healthy Adult Subjects
Pharmacokinetic Parameter [Zmax, 3-day and 5-day regimen parameters obtained from separate pharmacokinetic studies] | Azithromycin Regimen
Pharmacokinetic Parameter [Zmax, 3-day and 5-day regimen parameters obtained from separate pharmacokinetic studies] | Zmax [N=41] [N = 21 for AUC0–∞ and t1/2] | 3-day [Cmax, Tmax and AUC0–24 values for Day 1 only] [N=12] | 5-day [N=12]
Cmax (µg/mL) | 0.821 (0.281) | 0.441 (0.223) | 0.434 (0.202)
Tmax [Median (range)] (hr) | 5.0 (2.0–8.0) | 2.5 (1.0–4.0) | 2.5 (1.0–6.0)
AUC0–24 (µg∙hr/mL) | 8.62 (2.34) | 2.58 (0.84) | 2.60 (0.71)
AUC0–∞ [Total AUC for the 1-day, 3-day and 5-day regimens] (µg∙hr/mL) | 20.0 (6.66) | 17.4 (6.2) | 14.9 (3.1)
t1/2 (hr) | 58.8 (6.91) | 71.8 (14.7) | 68.9 (13.8)
SD = standard deviation
Cmax = maximum serum concentration
Tmax = time to Cmax
AUC = area under concentration vs. time curve
t1/2 = terminal serum half-life

Absorption

The bioavailability of Zmax relative to azithromycin immediate release (IR) (powder for oral suspension) was 83%. On average, peak serum concentrations were achieved approximately 2.5 hours later following Zmax administration and were lower by 57%, compared to 2 g azithromycin IR. Thus, single 2 g doses of Zmax and azithromycin IR are not bioequivalent and are not interchangeable.

Effect of food on absorption: A high-fat meal increased the rate and extent of absorption of a 2 g dose of Zmax (115% increase in Cmax, and 23% increase in AUC0–72) compared to the fasted state. A standard meal also increased the rate of absorption (119% increase in Cmax) and with less effect on the extent of absorption (12% increase in AUC0–72) compared to administration of a 2 g Zmax dose in the fasted state.

Effect of antacids: Following the administration of Zmax with an aluminum and magnesium hydroxide antacid, the rate and extent of azithromycin absorption were not altered.

Distribution

The serum protein binding of azithromycin is concentration dependent, decreasing from 51% at 0.02 µg/mL to 7% at 2 µg/mL. Following oral administration, azithromycin is widely distributed throughout the body with an apparent steady-state volume of distribution of 31.1 L/kg.

Azithromycin concentrates in fibroblasts, epithelial cells, macrophages, and circulating neutrophils and monocytes. Higher azithromycin concentrations in tissues than in plasma or serum have been observed. White blood cell and lung exposure data in humans following a single 2 g dose of Zmax in adults are shown in Table 3. Following a 2 g single dose of Zmax, azithromycin achieved higher exposure (AUC0–120) in mononuclear leukocytes (MNL) and polymorphonuclear leukocytes (PMNL) than in serum. The azithromycin exposure (AUC0–72) in lung tissue and alveolar cells (AC) was approximately 100 times that in serum; and the exposure in epithelial lining fluid (ELF) was also higher (approximately 2–3 times) than in serum. The clinical significance of this distribution data is unknown.

Table 3. Azithromycin Exposure Data in White Blood Cells and Lung Following a 2 g Single Dose of Zmax in Adults
A single 2 g dose of Zmax
WBC | Cmax (µg/mL) | AUC0–24 (µg∙hr/mL) | AUC0–120 (µg∙hr/mL) | Ct=120 [Azithromycin concentration at 120 hours after the start of dosing] (µg/mL)
MNL [Data are presented as mean (standard deviation)] | 116 (40.2) | 1790 (540) | 4710 (1100) | 16.2 (5.51)
PMNL | 146 (66.0) | 2080 (650) | 10000 (2690) | 81.7 (23.3)
LUNG | Cmax (µg/mL) | AUC0–24 (µg∙hr/mL) | AUC0–72 (µg∙hr/mL)
ALVEOLAR CELL [Cmax and AUC were calculated based on composite profile (n = 4 subjects/time point/formulation).] | 669 | 7028 | 20403 | -
ELF | 3.2 | 17.6 | 131 | -
 | Cmax (µg/g) | AUC0–24 (µg∙hr/g) | AUC0–72 (µg∙hr/g)
LUNG TISSUE | 37.9 | 505 | 1693 | -
Abbreviation: WBC: white blood cells; MNL: mononuclear leukocytes; PMNL: polymorphonuclear leukocytes; ELF: Epithelial lining fluid

Following a regimen of 500 mg of azithromycin tablets on the first day and 250 mg daily for 4 days, only very low concentrations were noted in cerebrospinal fluid (less than 0.01 µg/mL) in the presence of non-inflamed meninges.

Metabolism

In vitro and in vivo studies to assess the metabolism of azithromycin have not been performed.

Excretion

Serum azithromycin concentrations following a single 2 g dose of Zmax declined in a polyphasic pattern with a terminal elimination half-life of 59 hours. The prolonged terminal half-life is thought to be due to a large apparent volume of distribution.

Biliary excretion of azithromycin, predominantly as unchanged drug, is a major route of elimination. Over the course of a week, approximately 6% of the administered dose appears as unchanged drug in urine.

Special Populations

Renal Impairment

Azithromycin pharmacokinetics were investigated in 42 adults (21 to 85 years of age) with varying degrees of renal impairment. Following the oral administration of a single 1.0 g dose of azithromycin (4 × 250 mg capsules), the mean Cmax and AUC0–120 were 5.1% and 4.2% higher, respectively in subjects with GFR 10 to 80 mL/min compared to subjects with normal renal function (GFR >80 mL/min). The mean Cmax and AUC0–120 were 61% and 35% higher, respectively in subjects with GFR <10 mL/min compared to subjects with normal renal function. (See Renal Impairment (8.6).)

Hepatic Impairment

The pharmacokinetics of azithromycin in subjects with hepatic impairment has not been established.

Pediatric Patients

The pharmacokinetics of azithromycin were characterized following a single 60 mg/kg dose of Zmax in pediatric patients aged 3 months to 16 years. Although there was high inter-patient variability in systemic exposure (AUC and Cmax) across the age groups studied, individual azithromycin AUC and Cmax values in pediatric patients were comparable to or higher than those following administration of 2 g Zmax in adults (Table 4). (See Pediatric Use (8.4).)

Table 4. Mean (SD) Pharmacokinetic Parameters for Azithromycin Following Administration of a Single Dose of Zmax (60 mg/kg, maximum dose of 2 g) to Pediatric Subjects Aged 3 Months to 16 Years
Treatment Group | Pharmacokinetic Parameters
Treatment Group | Cmax (µg/mL) | Tmax [Median (range) presented only for Tmax] (hr) | AUC(0–24) (µg∙hr/mL) | AUC(0–∞) (µg∙hr/mL)
Group 1 (N = 6) [3 to 18 months] | 0.74 (0.20) | 3 (3–3) | 6.29 (1.17) | 14.1 (2.16) (n = 3)
Group 2 [High mean values were driven by 2 subjects with high exposure] (N = 6) [>18 to 36 months] | 1.88 (0.50) | 3 (3–3) | 19.7 (5.35) | 37.3 (12.9) (n = 5)
Group 3 (N = 6) [>36 to 48 months] | 1.23 (0.42) | 3 (3–6) | 12.9 (3.79) | 22.4 (5.96)
Group 4 (N = 6) [>48 months to 8 years] | 1.13 (0.34) | 3 (3–6) | 13.0 (4.21) | 22.2 (6.89)
Group 5 (N = 6) [>8 to 12 years] | 1.65 (0.38) | 3 (3–6) | 16.0 (4.99) | 30.1 (10.7)
Group 6 (N = 6) [>12 to 16 years] | 0.98 (0.35) | 3 (3–6) | 11.0 (4.78) | 21.3 (9.37)
Pooled 1–6 (N = 36) [On an empty stomach] | 1.27 (0.53) | 3 (3–6) | 13.1 (5.78) | 25.2 (10.7) (n = 32)
Group 7 [One subject vomited immediately after dosing and discontinued from the study] (N = 7) [Fed; 18 months to 8 years] | 1.41 (0.62) | 3 (1.5–3.1) | 7.43 (3.00) | 18.9 (3.57) (n = 3)
Empty stomach = dosed with Zmax at least 1 hour before or 2 hours after a meal (Groups I–VI)
Fed = dosed with Zmax within 5 minutes of consuming an age-appropriate high-fat breakfast (Group VII)

Gender

The impact of gender on the pharmacokinetics of azithromycin has not been evaluated for Zmax. However, previous studies have demonstrated no significant differences in the disposition of azithromycin between male and female subjects.

Pharmacokinetic Interaction Studies

A drug interaction study was performed with Zmax and antacids. All other drug interaction studies were performed with azithromycin immediate release (IR) formulations (capsules and tablets, doses ranging from 500 to 1200 mg) and other drugs likely to be co-administered. The effects of co-administration of azithromycin on the pharmacokinetics of other drugs are shown in Table 5 and the effects of other drugs on the pharmacokinetics of azithromycin are shown in Table 6.

When used at therapeutic doses, azithromycin IR had a minimal effect on the pharmacokinetics of atorvastatin, carbamazepine, cetirizine, didanosine, efavirenz, fluconazole, indinavir, midazolam, nelfinavir, sildenafil, theophylline (intravenous and oral), triazolam, trimethoprim/sulfamethoxazole or zidovudine (Table 5). Although the drug interaction studies were not conducted with Zmax, similar modest effect as observed with IR formulation are expected since the total exposure to azithromycin is comparable for Zmax and other azithromycin IR regimens. Therefore, no dosage adjustment of drugs listed in Table 5 is recommended when co-administered with Zmax.

Nelfinavir significantly increased the Cmax and AUC of azithromycin following co-administration with azithromycin IR 1200 mg (Table 6). However, no dose adjustment of azithromycin is recommended when Zmax is co-administered with nelfinavir.

Pharmacokinetic and/or pharmacodynamic interactions with the drugs listed below have not been reported in clinical trials with azithromycin; however, no specific drug interaction studies have been performed to evaluate potential drug-drug interaction. Nonetheless, pharmacokinetic and/or pharmacodynamic interactions with these drugs have been observed with other macrolide products. Until further data are developed, careful monitoring of patients is advised when azithromycin and these drugs are used concomitantly: digoxin, ergotamine or dihydroergotamine, cyclosporine, hexobarbital and phenytoin.

Table 5. Drug Interactions: Pharmacokinetic Parameters of Co-administered Drugs in the Presence of Azithromycin
Co-administered Drug | Dose of Co-administered Drug | Dose of Azithromycin [Refers to azithromycin capsules and tablets unless specified] | n | Ratio (with/without Azithromycin) of Co-administered Drug Pharmacokinetic Parameters (90% CI); No Effect = 1.00
Co-administered Drug | Dose of Co-administered Drug | Dose of Azithromycin [Refers to azithromycin capsules and tablets unless specified] | n | Mean Cmax | Mean AUC
Atorvastatin | 10 mg/day × 8 days | 500 mg/day PO on days 6–8 | 12 | 0.83 (0.63 to 1.08) | 1.01 (0.81 to 1.25)
Carbamazepine | 200 mg/day × 2 days, then 200 mg BID × 18 days | 500 mg/day PO for days 16–18 | 7 | 0.97 (0.88 to 1.06) | 0.96 (0.88 to 1.06)
Cetirizine | 20 mg/day × 11 days | 500 mg PO on day 7, then 250 mg/day on days 8–11 | 14 | 1.03 (0.93 to 1.14) | 1.02 (0.92 to 1.13)
Didanosine | 200 mg PO BID × 21 days | 1,200 mg/day PO on days 8–21 | 6 | 1.44 (0.85 to 2.43) | 1.14 (0.83 to 1.57)
Efavirenz | 400 mg/day × 7 days | 600 mg PO on day 7 | 14 | 1.04 [90% confidence interval not reported] | 0.95
Fluconazole | 200 mg PO single dose | 1,200 mg PO single dose | 18 | 1.04 (0.98 to 1.11) | 1.01 (0.97 to 1.05)
Indinavir | 800 mg TID × 5 days | 1,200 mg PO on day 5 | 18 | 0.96 (0.86 to 1.08) | 0.90 (0.81 to 1.00)
Midazolam | 15 mg PO on day 3 | 500 mg/day PO × 3 days | 12 | 1.27 (0.89 to 1.81) | 1.26 (1.01 to 1.56)
Nelfinavir | 750 mg TID × 11 days | 1,200 mg PO on day 9 | 14 | 0.90 (0.81 to 1.01) | 0.85 (0.78 to 0.93)
Sildenafil | 100 mg on days 1 and 4 | 500 mg/day PO × 3 days | 12 | 1.16 (0.86 to 1.57) | 0.92 (0.75 to 1.12)
Theophylline | 4 mg/kg IV on days 1, 11, 25 | 500 mg PO on day 7, then 250 mg/day on days 8–11 | 10 | 1.19 (1.02 to 1.40) | 1.02 (0.86 to 1.22)
Theophylline | 300 mg PO BID × 15 days | 500 mg PO on day 6, then 250 mg/day on days 7–10 | 8 | 1.09 (0.92 to 1.29) | 1.08 (0.89 to 1.31)
Triazolam | 0.125 mg on day 2 | 500 mg PO on day 1, then 250 mg/day on day 2 | 12 | 1.06 | 1.02
Trimethoprim/ Sulfamethoxazole | 160 mg/800 mg/day PO × 7 days | 1,200 mg PO on day 7 | 12 | 0.85 (0.75 to 0.97)/ 0.90 (0.78 to 1.03) | 0.87 (0.80 to 0.95)/ 0.96 (0.88 to 1.03)
Zidovudine | 500 mg/day PO × 21 days | 600 mg/day PO × 14 days | 5 | 1.12 (0.42 to 3.02) | 0.94 (0.52 to 1.70)
Zidovudine | 500 mg/day PO × 21 days | 1,200 mg/day PO × 14 days | 4 | 1.31 (0.43 to 3.97) | 1.30 (0.69 to 2.43)

Table 6. Drug Interactions: Pharmacokinetic Parameters of Azithromycin in the Presence of Co-administered Drugs
Co-administered Drug | Dose of Co-administered Drug | Dose of Azithromycin [Refers to azithromycin capsules and tablets unless specified] | n | Ratio (with/without co-administered drug) of Azithromycin Pharmacokinetic Parameters (90% CI); No Effect = 1.00
Co-administered Drug | Dose of Co-administered Drug | Dose of Azithromycin [Refers to azithromycin capsules and tablets unless specified] | n | Mean Cmax | Mean AUC
Efavirenz | 400 mg/day × 7 days | 600 mg PO on day 7 | 14 | 1.22 (1.04 to 1.42) | 0.92 [90% confidence interval not reported]
Fluconazole | 200 mg PO single dose | 1,200 mg PO single dose | 18 | 0.82 (0.66 to 1.02) | 1.07 (0.94 to 1.22)
Nelfinavir | 750 mg TID × 11 days | 1,200 mg PO on day 9 | 14 | 2.36 (1.77 to 3.15) | 2.12 (1.80 to 2.50)
Aluminum and Magnesium hydroxide | 20 mL regular strength, single dose | 2 g Zmax, single dose | 39 | 0.99 (0.93 to 1.06) | 0.99 (0.92 to 1.08)

12.4 Microbiology

Mechanism of Action

Azithromycin acts by binding to the 50S ribosomal subunit of susceptible microorganisms, thus interfering with microbial protein synthesis. Nucleic acid synthesis is not affected.

Spectrum of Activity

Azithromycin has been shown to be active against most isolates of the following microorganisms, both in vitro and in clinical infections as described in the INDICATIONS AND USAGE section.

Aerobic and facultative Gram-positive microorganisms
Streptococcus pneumoniae

NOTE: Erythromycin- and penicillin-resistant Gram-positive isolates may demonstrate cross-resistance to azithromycin.

Aerobic and facultative Gram-negative microorganisms
Haemophilus influenzae
Moraxella catarrhalis

Beta-lactamase production should not affect azithromycin activity.

"Other" microorganisms
Chlamydophila pneumoniae
Mycoplasma pneumoniae

The following in vitro data are available, but their clinical significance is unknown.

At least 90% of the following microorganisms exhibit an in vitro minimum inhibitory concentration (MIC) less than or equal to the azithromycin susceptible breakpoints of <4 µg/mL. However, the safety and effectiveness of azithromycin in treating clinical infections due to these microorganisms have not been established in adequate and well-controlled trials.

Aerobic and facultative Gram-positive microorganisms
Staphylococcus aureus
Streptococcus agalactiae
Streptococcus pyogenes
Streptococci (Groups C, F, G)
Viridans group streptococci

Aerobic and facultative Gram-negative microorganisms
Bordetella pertussis
Legionella pneumophila

Anaerobic microorganisms
Peptostreptococcus species
Prevotella bivia

"Other" microorganisms
Ureaplasma urealyticum

Susceptibility Testing Methods:

When available, the clinical microbiology laboratory should provide cumulative results of in vitro susceptibility test results for antimicrobial drugs used in local hospitals and practice areas to the physician as periodic reports that describe the susceptibility profile of nosocomial and community-acquired pathogens. These reports should aid the physician in selecting the most effective antimicrobial.

Dilution techniques:

Quantitative methods are used to determine antimicrobial minimum inhibitory concentrations (MICs). These MICs provide estimates of the susceptibility of bacteria to antimicrobial compounds. The MICs should be determined using a standardized procedure. Standardized procedures are based on a dilution method^1,3 (broth or agar) or equivalent with standardized inoculum concentrations and standardized concentrations of azithromycin powder. The MIC values should be interpreted according to criteria provided in Table 7.

Diffusion techniques:

Quantitative methods that require measurement of zone diameters also provide reproducible estimates of the susceptibility of bacteria to antimicrobial compounds. One such standardized procedure^2,3 requires the use of standardized inoculum concentrations. This procedure uses paper disks impregnated with 15-µg azithromycin to test the susceptibility of microorganisms to azithromycin. The disk diffusion interpretive criteria are provided in Table 7.

Table 7. Susceptibility Test Result Interpretive Criteria for Azithromycin
 | Minimum Inhibitory Concentrations (µg/mL) |  |  | Disk Diffusion (zone diameters in mm)
Pathogen | S | I | R [The current absence of data on resistant strains precludes defining any category other than "susceptible." If strains yield MIC results other than susceptible, they should be submitted to a reference laboratory for further testing.] | S | I | R
Haemophilus influenzae | ≤ 4 | -- | -- | ≥ 12 | -- | --
Streptococcus pneumoniae | ≤ 0.5 | 1 | ≥ 2 | ≥ 18 | 14–17 | ≤ 13

No interpretive criteria have been established for testing Moraxella catarrhalis. This species is not usually tested.

A report of "susceptible" indicates that the pathogen is likely to be inhibited if the antimicrobial compound reaches the concentrations usually achievable. A report of "intermediate" indicates that the result should be considered equivocal, and, if the microorganism is not fully susceptible to alternative, clinically feasible drugs, the test should be repeated. This category implies possible clinical applicability in body sites where the drug is physiologically concentrated or in situations where high dosage of drug can be used. This category also provides a buffer zone, which prevents small uncontrolled technical factors from causing major discrepancies in interpretation. A report of "resistant" indicates that the pathogen is not likely to be inhibited if the antimicrobial compound reaches the concentrations usually achievable; other therapy should be selected.

Quality Control:

Standardized susceptibility test procedures require the use of quality control microorganisms to determine if the test was performed correctly. Standard azithromycin powder should provide the range of values noted in Table 8. Quality control (QC) microorganisms are specific strains of organisms with intrinsic biological properties. QC strains are very stable strains, which will give a standard and repeatable susceptibility pattern. The specific strains used for microbiological quality control are not clinically significant.

Table 8. Acceptable Quality Control Ranges for Azithromycin
QC Strain | Minimum Inhibitory Concentrations (µg/mL) | Disk Diffusion (zone diameters in mm)
Haemophilus influenzae ATCC 49247 | 1.0–4.0 | 13–21
Streptococcus pneumoniae ATCC 49619 | 0.06–0.25 | 19–25

13 NONCLINICAL TOXICOLOGY

13. 1 Carcinogenesis, Mutagenesis, Impairment of Fertility

Long-term studies in animals have not been performed to evaluate carcinogenic potential. Azithromycin has shown no mutagenic potential in standard laboratory tests: mouse lymphoma assay, human lymphocyte clastogenic assay, and mouse bone marrow clastogenic assay. No evidence of impaired fertility due to azithromycin was found in rats given daily doses up to 10 mg/kg (approximately 0.05 times the single 2 g oral adult human dose on a mg/m^2 basis).

13. 2 Animal Toxicology and/or Pharmacology

Phospholipidosis (intracellular phospholipid accumulation) has been observed in some tissues of mice, rats, and dogs given multiple doses of azithromycin. It has been demonstrated in numerous organ systems (e.g., eye, dorsal root ganglia, liver, gallbladder, kidney, spleen, and/or pancreas) in dogs treated with azithromycin at doses which, expressed on the basis of mg/m^2, are approximately one-sixth the recommended adult dose, and in rats treated at doses approximately one-fourth the recommended adult dose. This effect has been shown to be reversible after cessation of azithromycin treatment. Based on the pharmacokinetic data, phospholipidosis has been seen in the rat (50 mg/kg/day dose) at the observed maximal plasma concentration of 1.3 µg/mL (1.6 times the observed Cmax of 0.821 µg/mL at the adult dose of 2 g.) Similarly, it has been shown in the dog (10 mg/kg/day dose) at the observed maximal serum concentration of 1 µg/mL (1.2 times the observed Cmax of 0.821 µg/mL at the adult dose of 2 g).

Phospholipidosis was also observed in neonatal rats dosed for 18 days at 30 mg/kg/day, which is less than the pediatric dose of 60 mg/kg on a mg/m^2 basis, but was not observed in neonatal rats treated for 10 days at 40 mg/kg/day with mean maximal serum concentrations of 1.86 µg/ml, approximately 1.5 times the Cmax of 1.27 µg/ml at the pediatric dose. Phospholipidosis has been observed in neonatal dogs (10 mg/kg/day) at maximum mean whole blood concentrations of 3.54 µg/ml, approximately 3 times the pediatric dose Cmax.

The significance of the finding for animals and for humans is unknown.

14 CLINICAL STUDIES

Acute Bacterial Maxillary Sinusitis

Adult subjects with a diagnosis of acute bacterial maxillary sinusitis were evaluated in a randomized, double-blind, multicenter study; a maxillary sinus tap was performed on all subjects at baseline. Clinical evaluations were conducted for all subjects at the TOC visit, 7 to 14 days post-treatment. Two hundred seventy (270) subjects were treated with a single 2 g oral dose of Zmax and 268 subjects were treated with levofloxacin, 500 mg orally QD for 10 days. A subject was considered a cure if signs and symptoms related to the acute infection had resolved, or if clinical improvement was such that no additional antibiotics were deemed necessary. The clinical response for the primary population, Clinical Per Protocol Subjects, is presented below.

 | ZMAX | LEVOFLOXACIN
RESPONSE AT TOC | N = 255 | N = 254
CURE | 241 (94.5%) | 236 (92.9%)
FAILURE | 14 (5.5%) | 18 (7.1%)

Clinical response by pathogen in the Bacteriologic Per Protocol population is presented below.

 | Zmax |  | Levofloxacin
Pathogen | N | Cure | N | Cure
S. pneumoniae | 37 | 36 (97.3%) | 39 | 36 (92.3%)
H. influenzae | 27 | 26 (96.3%) | 30 | 30 (100.0%)
M. catarrhalis | 8 | 8 (100.0%) | 11 | 10 (90.9%)

Community-Acquired Pneumonia

Adult subjects with a diagnosis of mild-to-moderate community-acquired pneumonia were evaluated in two, randomized, double-blind, multicenter studies. In both studies, clinical and microbiologic evaluations were conducted for all subjects at the Test of Cure (TOC) visit, 7 to 14 days post-treatment. In the first study, 247 subjects were treated with a single 2 g oral dose of Zmax and 252 subjects were treated with clarithromycin extended release, 1 g orally QD for 7 days. In the second study, 211 subjects were treated with a single 2.0 g oral dose of Zmax and 212 subjects were treated with levofloxacin, 500 mg orally QD for 7 days. A patient was considered a cure if signs and symptoms related to the acute infection had resolved, or if clinical improvement was such that no additional antibiotics were deemed necessary; in addition, the chest x-ray performed at the TOC visit was to be either improved or stable. The clinical response at TOC for the primary population, Clinical Per Protocol Subjects, is presented in the table below.

 | ZMAX | COMPARATOR
ZMAX VS. CLARITHROMYCIN EXTENDED RELEASE | N=202 | N=209
CURE | 187 (92.6%) | 198 (94.7%)
FAILURE | 15 (7.4%) | 11 (5.3%)
ZMAX VS. LEVOFLOXACIN | N=174 | N=189
CURE | 156 (89.7%) | 177 (93.7%)
FAILURE | 18 (10.3%) | 12 (6.3%)

Clinical response by pathogen in the Bacteriologic Per Protocol population, across both studies, is presented below:

Pathogen | Zmax |  | Comparators
 | N | Cure | N | Cure
S. pneumoniae | 33 | 28 (84.8%) | 39 | 35 (89.7%)
H. influenzae | 30 | 28 (93.3%) | 34 | 31 (91.2%)
C. pneumoniae | 40 | 37 (92.5%) | 53 | 50 (94.3%)
M. pneumoniae | 33 | 30 (90.9%) | 39 | 38 (97.4%)

15 REFERENCES

1. Clinical and Laboratory Standards Institute. Methods for Dilution Antimicrobial Susceptibility Tests for Bacteria That Grow Aerobically; Approved Standard – Seventh Edition. 2006. CLSI Document M7-A7 [ISBN 1-56238-587-9]. CLSI, 940 West Valley Road, Suite 1400, Wayne, Pennsylvania 19087-1898 USA, 2006.
2. Clinical and Laboratory Standards Institute. Performance Standards for Antimicrobial Disk Susceptibility Tests; Approved Standard – Ninth Edition. CLSI Document M2-A9 (ISBN 1-56238-586-0). CLSI, 940 West Valley Road, Suite 1400, Wayne, Pennsylvania 19087-1898 USA, 2006.
3. Clinical and Laboratory Standards Institute. Performance Standards for Antimicrobial Susceptibility Testing; Eighteenth Informational Supplement. 2008. CLSI Document M100-S18 [ISBN 1-56238-653-0]. CLSI, 940 West Valley Road, Suite 1400, Wayne, Pennsylvania 19087-1898 USA, 2008.

16 HOW SUPPLIED/STORAGE AND HANDLING

NDC 21695-444-60 for pediatric use is supplied in bottles containing 2 g of azithromycin and should be constituted with 60 mL of water.

Storage

Before constitution, store dry powder at or below 30°C (86°F).

After constitution, store suspension at 25°C (77°F); excursions permitted to 15–30°C (59–86°F) [see USP Controlled Room Temperature]. Do not refrigerate or freeze.

Constituted suspension should be consumed within 12 hours. For adult patients, the entire bottle should be consumed. For pediatric patients, any suspension remaining after dosing MUST be discarded.

17 PATIENT COUNSELING INFORMATION

See FDA-approved Patient Labeling (17.2)

17.1 General Patient Counseling

- Patients should be instructed to take Zmax on an empty stomach (at least 1 hour before or 2 hours following a meal).
- To ensure accurate dosing for children, use of a dosing spoon, medicine syringe, or cup is recommended.
- Patients should be told that Zmax needs time to work, so the patient may not feel better right away. If the patient's symptoms do not improve in a few days, the patient or their guardian should call their doctor.
- Patients should be instructed to immediately contact a physician if any signs of an allergic reaction occur.
- Diarrhea is a common problem caused by antibiotics which usually ends when the antibiotic is discontinued. Sometimes after starting treatment with antibiotics, patients can develop watery and bloody stools (with or without stomach cramps and fever) even as late as two or more months after having taken the last dose of the antibiotic. If this occurs, patients should contact their physician as soon as possible.
- Patients who vomit within the first hour should contact their health care provider about further treatment.
- Keep bottle tightly closed. Store at room temperature. Use within 12 hours of constitution. Shake bottle well before use. Adult patients should consume the entire contents of the bottle; pediatric patients should take the recommended dose and MUST discard any unused portion.
- Patients should be advised that Zmax may be taken without regard to antacids containing magnesium hydroxide and/or aluminum hydroxide.

Patients should be counseled that antibacterial drugs including Zmax should only be used to treat bacterial infections. They do not treat viral infections (e.g., the common cold). Not taking the complete prescribed dose may (1) decrease the effectiveness of the immediate treatment and (2) increase the likelihood that bacteria will develop resistance and will not be treatable by Zmax or other antibacterial drugs in the future.

PATIENT INFORMATION

Read the Patient Information that comes with Zmax ® carefully before you or your child take it. This leaflet does not take the place of talking with your doctor about you or your child's medical condition or treatment. Only your doctor can decide if Zmax is right for you or your child.

What is Zmax?

Zmax is an antibiotic that kills certain bacteria. Zmax is dosed differently from other antibiotics.

You take just one dose, one time.

- Day 1: Take Zmax in one dose. Zmax starts working.
- Days 2 – 3: As with most antibiotics, you may not feel better right away.
- After Day 3: Zmax continues to work over time. If your symptoms are not better, call your doctor.

Zmax is used in adults and in children over the age of 6 months against bacteria to treat certain kinds of pneumonia (lung infections)

Zmax is used in adults against bacteria to treat sinus infections.

Zmax only works against bacteria. It does not work against viruses, like the common cold or flu.

Zmax has not been studied in children under 6 months of age.

Who should not take Zmax?

- You or your child should not take Zmax if allergic to:
  - anything in Zmax. See the end of this leaflet for a complete list of ingredients in Zmax.
  - antibiotics like erythromycin or telithromycin (Ketek®).

Talk with your doctor or pharmacist if you have questions about your medicine allergies.

Before you start Zmax...

Tell your doctor about all your or your child's medical problems including if you or your child :

- have liver problems.
- have kidney problems.
- have myasthenia gravis.
- are pregnant, or might be pregnant. It is not known if Zmax could harm your baby.
- are breast-feeding.

Tell your doctor about all the medicines you take, including prescription and non-prescription medicines, vitamins and herbal supplements. Especially tell your doctor if you or your child are taking warfarin (Coumadin®, Jantoven)

Know the medicines you take. Keep a list of your medicines and show it to your doctor or pharmacist when you get a new prescription.

Do I need to prepare Zmax?

- If you get Zmax in liquid form, it is ready to take.
- If you get Zmax as dry powder, you must add water to the bottle before you take it. To prepare Zmax:
  1. Open the bottle: To open the bottle, press down on the cap and twist.
  2. Use a measuring cup to add 60 mL (1/4 cup) water to the Zmax bottle.
  3. Tightly close the bottle and shake to mix it.

How do I take Zmax?

- Keep Zmax at room temperature between 59ºF to 86ºF (15º to 30ºC).
- Shake the bottle well before using.
- Take Zmax or give it to your child within 12 hours after it has been prepared by the pharmacy or you add water to the powder.
- Take Zmax or give it to your child exactly how your doctor prescribes it. This will help to treat you or your child's infection and decrease the chance that Zmax or other antibiotics will not work to treat infections in the future.
  - Adults: take all the medicine in the bottle.
  - Children: give your child the amount of Zmax prescribed by your doctor and throw away the rest of the medicine.
  - To be sure that you give your child the right dose of Zmax, use a dosing spoon, medicine syringe, or cup.
- Take Zmax on an empty stomach (at least 1 hour before eating or 2 hours after eating).
- You can take antacids with Zmax.
- If you or your child throws up (vomits) within one hour of taking Zmax, call your doctor right away to see if more medicine is needed. Do not give your child more Zmax unless your doctor tells you to.
- If your child takes too much Zmax, call your doctor right away or go to the nearest hospital emergency room.

How will I know Zmax is working?

Zmax needs time to work, so you or your child may not feel better right away. If you or your child's symptoms do not get better in a few days, call your doctor.

What are possible side effects of Zmax?

Zmax may cause serious side effects. These happened in a small number of patients. Call your doctor right away or get emergency treatment if you or your child have any of the following:

- Serious allergic reaction or serious skin reaction: Get emergency help right away if you or your child has:
  - Hives, skin rash, sores in your mouth, or your skin blisters and peels
  - Trouble swallowing,
  - Swelling of your face, eyes, lips, tongue or throat
  - Wheezing or trouble breathing

These symptoms could go away and then come back.

- Diarrhea: Call your doctor right away if you have diarrhea that does not go away, is severe, watery, or has blood in it. Diarrhea can occur as late as two or more months after you take an antibiotic such as Zmax.
- Abnormal heart rhythm. Tell your doctor right away if you or your child feel your heart beating in your chest or an abnormal heart beat, get dizzy or faint. This has been seen with other antibiotics like Zmax.

The most common side effects in adults are:

- Diarrhea/loose stools
- Nausea
- Stomach pain
- Headache
- Vomiting

The most common side effects in children are:

- Vomiting
- Diarrhea/loose stools
- Nausea
- Stomach pain

Tell your doctor if you have any side effects that bother your or your child, or that does not go away.

These are not all of the possible side effects with Zmax. For a list of all reported side effects, ask your doctor or pharmacist.

General information about Zmax

Doctors sometimes prescribe medicines for conditions that are not in the patient leaflets. Do not use Zmax for anything other than what your doctor prescribed. Do not give it to other people, even if they have the same symptoms you have. It may harm them.

This Patient Information leaflet is a summary of the most important information about Zmax. For more information, talk with your doctor. You can ask your doctor or pharmacist for information about Zmax that is written for healthcare professionals. For more information, go to our website at www.zmaxinfo.com or call 1-800-438-1985.

What is in Zmax?

Active ingredient: azithromycin dihydrate

Inactive ingredients: glyceryl behenate, poloxamer 407, sucrose, sodium phosphate tribasic anhydrous, magnesium hydroxide, hydroxypropyl cellulose, xanthan gum, colloidal silicon dioxide, titanium dioxide, artificial cherry flavor, and artificial banana flavor

Brand names are registered trademarks of their respective owners.
Coumadin® is a registered trademark of Bristol-Myers Squibb, Inc.
Ketek® is a registered trademark of Aventis Pharmaceuticals Inc.

LAB-0384-3.0
June 2009

Repackaged by:

Rebel Distributors Corp

Thousand Oaks, CA 91320